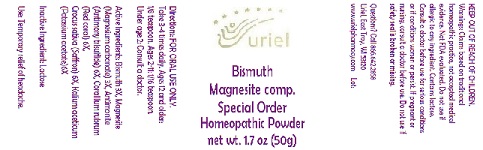 DRUG LABEL: Bismuth Magnesite comp.
NDC: 48951-8307 | Form: POWDER
Manufacturer: Uriel Pharmacy Inc.
Category: homeopathic | Type: HUMAN OTC DRUG LABEL
Date: 20180423

ACTIVE INGREDIENTS: BISMUTH 3 [hp_X]/1 g; ANTIMONY TRISULFIDE 6 [hp_X]/1 g; SAFFRON 6 [hp_X]/1 g; CORALLIUM RUBRUM EXOSKELETON 6 [hp_X]/1 g; MAGNESITE 3 [hp_X]/1 g; POTASSIUM ACETATE 6 [hp_X]/1 g
INACTIVE INGREDIENTS: LACTOSE 1 [hp_X]/1 g

Bismuth Magnesite comp. Special Order

INDICATIONS AND USAGE

Directions: FOR ORAL USE ONLY.

DOSAGE AND ADMINISTRATION

Take 3-4 times daily. Ages 12 and older:
1/8 teaspoon. Ages 2-11: 1/16 teaspoon.
Under age 2: Consult a doctor.

ACTIVE INGREDIENT

Active Ingredients: Bismuth 3X, Magnesite (Magnesium carbonate) 3X, Antimonite (Antimony trisulfide) 6X, Corallium rubrum (Red coral) 6X,
Crocus sativa (Saffron) 6X, Kalium aceticum (Potassium acetate)6X

Inactive Ingredient: Lactose

PURPOSE

Use: Temporary relief of headache.

KEEP OUT OF REACH OF CHILDREN

WARNINGS

Warnings: Claims based on traditional homeopathic practice, not accepted medical evidence. Not FDA evaluated. Do not use if allergic to any ingredient. Contains lactose. Consult a doctor before use for serious conditions or if conditions worsen or persist. If pregnant or nursing, consult a doctor before use. Do not use if safety seal is broken or missing.

Questions? Call 866.642.2858
Uriel, East Troy, WI 53120
www.urielpharmacy.com